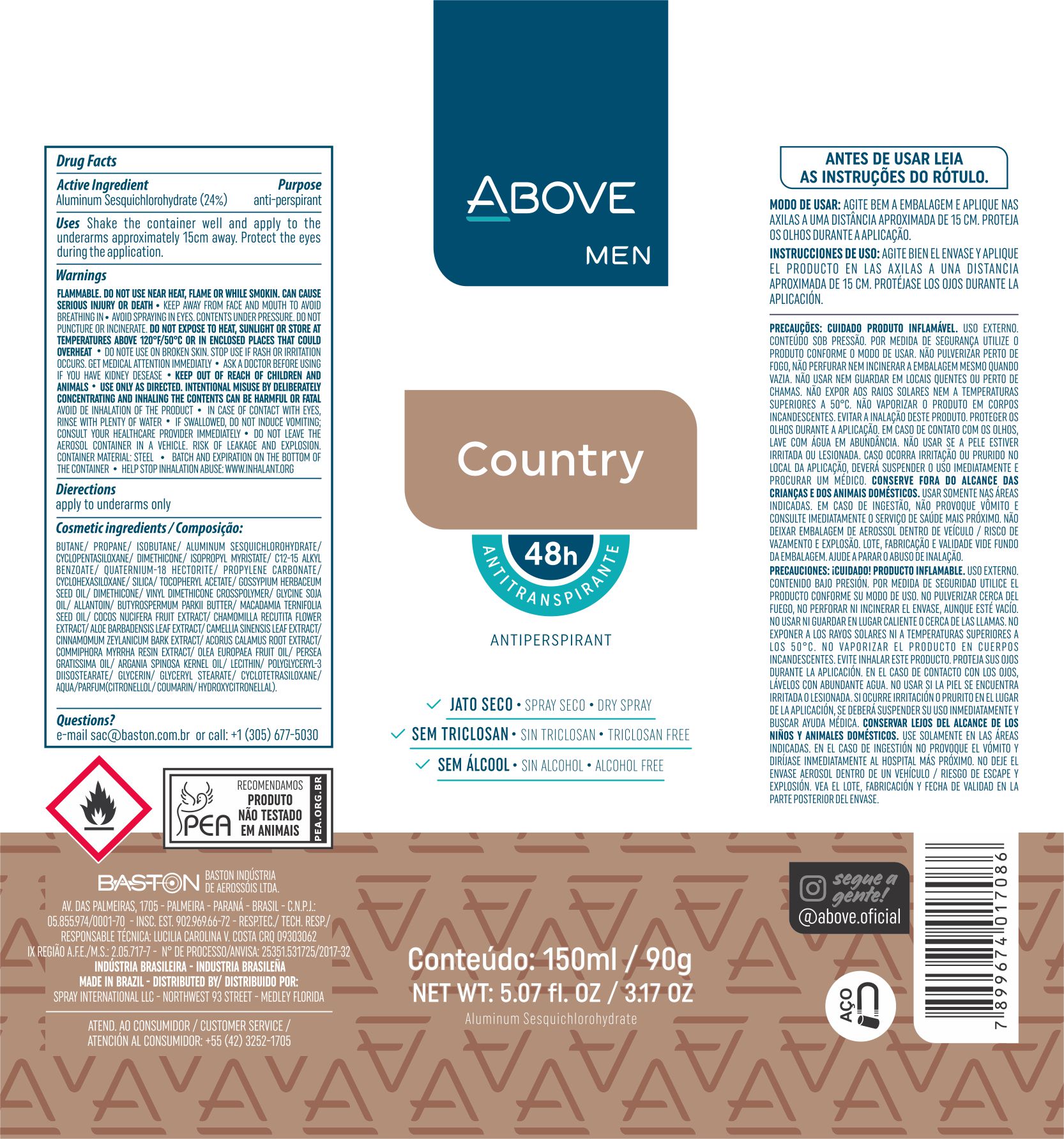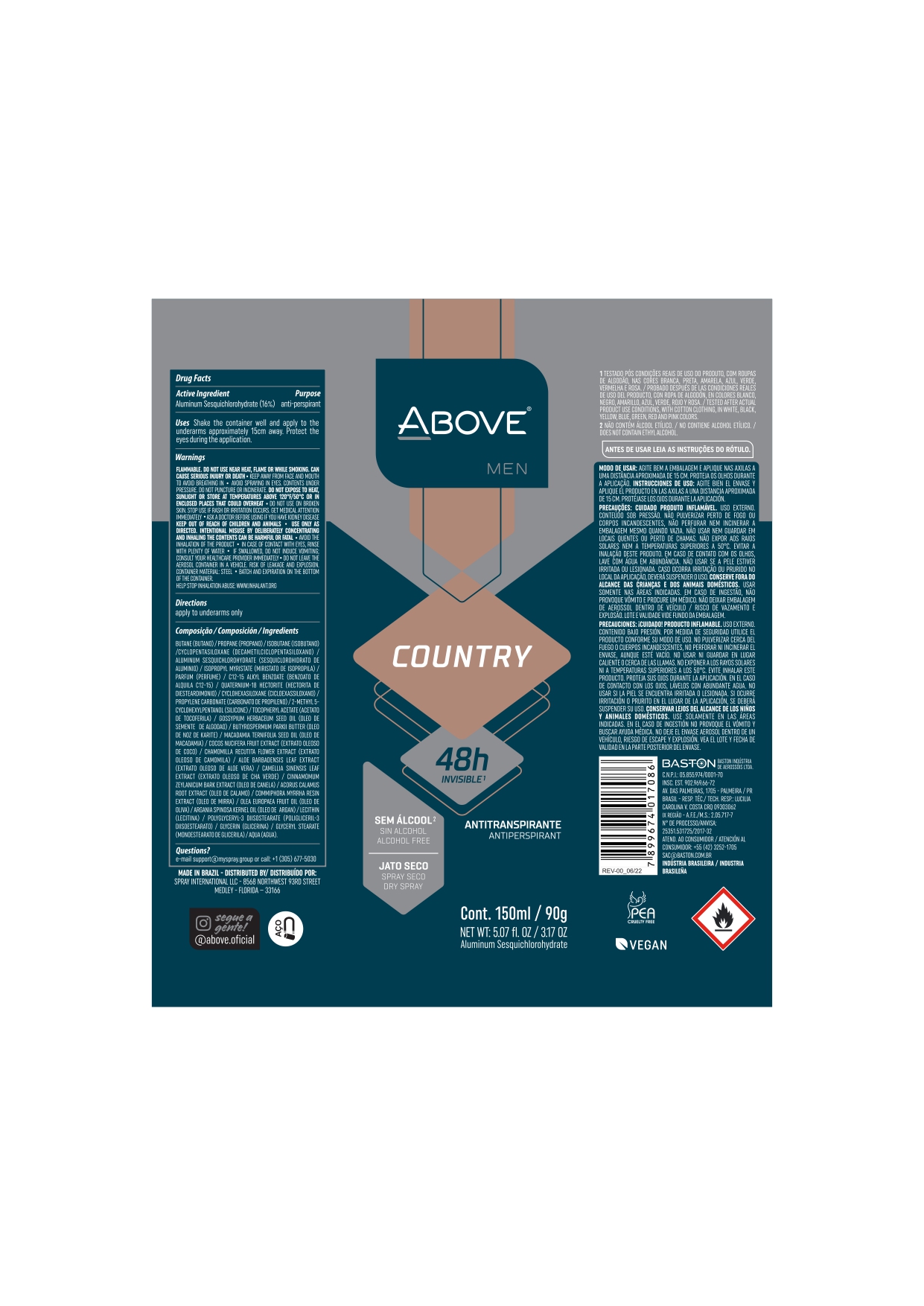 DRUG LABEL: Antiperspirant  Above Country
NDC: 73306-1102 | Form: AEROSOL, SPRAY
Manufacturer: Baston Industria de Aerossóis Ltda
Category: otc | Type: HUMAN OTC DRUG LABEL
Date: 20241226

ACTIVE INGREDIENTS: ALUMINUM SESQUICHLOROHYDRATE 24 g/100 g
INACTIVE INGREDIENTS: ISOBUTANE; PROPANE; ALPHA-TOCOPHEROL ACETATE; POLYGLYCERYL-3 DIISOSTEARATE; BUTANE; GLYCERYL MONOSTEARATE; WATER; SHEA BUTTER; PROPYLENE CARBONATE; MYRRH OIL; CHAMOMILE; GREEN TEA LEAF; ALOE VERA LEAF; ALLANTOIN; CYCLOMETHICONE 5; DIMETHICONE; GLYCERIN; LEVANT COTTON SEED; SILICA DIMETHYL SILYLATE; COCONUT; ACORUS CALAMUS ROOT; AVOCADO OIL; MACADAMIA OIL; ISOPROPYL MYRISTATE; CINNAMON BARK OIL; LECITHIN, SOYBEAN; VINYL DIMETHICONE/METHICONE SILSESQUIOXANE CROSSPOLYMER; DISTEARDIMONIUM HECTORITE; ARGAN OIL

Antiperspirant Above Country aerosol